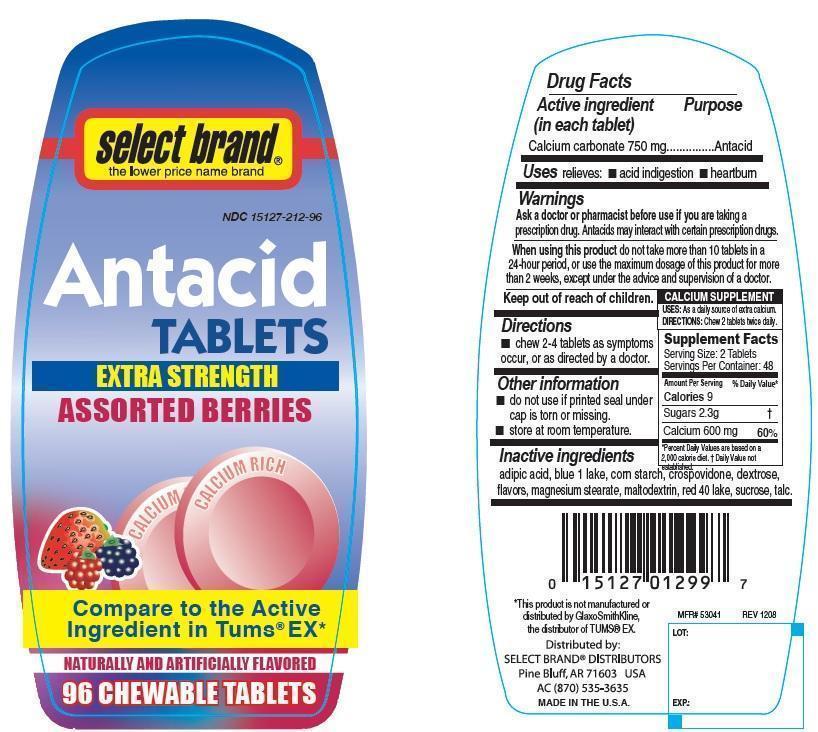 DRUG LABEL: Select Brand Antacid Assorted Berries
NDC: 15127-212 | Form: TABLET, CHEWABLE
Manufacturer: Select Brand
Category: otc | Type: HUMAN OTC DRUG LABEL
Date: 20140829

ACTIVE INGREDIENTS: CALCIUM CARBONATE 750 mg/1 1
INACTIVE INGREDIENTS: ADIPIC ACID; STARCH, CORN; CROSPOVIDONE; DEXTROSE; FD&C BLUE NO. 1; FD&C RED NO. 40; MAGNESIUM STEARATE; MALTODEXTRIN; SUCROSE; TALC

Select Brand antacid Extra strength Assorted Berries

Active ingredient (in each tablet)

Calcium carbonate 750 mg

Purpose

Antacid

Uses

relieves

- acid indigestion
- heartburn

Warnings

Ask a doctor or pharmacist before use if you are

taking a prescription drug. Antacids may interact with certain prescription drugs.

When using this product

do not take more than 10 tablets in a 24-hour period, or use the maximum dosage of this product for more than 2 weeks, except under the advice and supervision of the a doctor.

Keep out of reach of children

Directions

- chew 2-4 tablets as symptoms occur, or as directed by a doctor.

Other information

- do not use if printed seal under cap is torn or missing
- store at room temperature

Inactive ingredients

adipic acid, corn starch, crospovidone, dextrose, blue 1 lake, red 40 lake, flavors, magnesium stearate, maltodextrin, sucrose, talc

Principal Display Panel

Select Brand

Compare to the Active ingredient in Tums® EX

Antacid Tablets

Extra Strength

Assorted Berries

Naturally and Artificially Flavored

96 CHEWABLE TABLETS